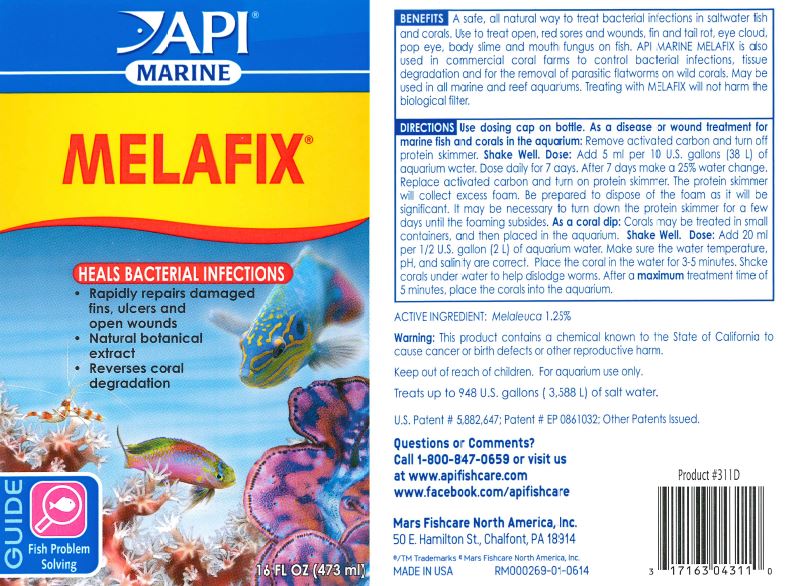 DRUG LABEL: API MARINE MELAFIX
NDC: 17163-311 | Form: LIQUID
Manufacturer: MARS FISHCARE NORTH AMERICA, INC.
Category: animal | Type: OTC ANIMAL DRUG LABEL
Date: 20191219

ACTIVE INGREDIENTS: CAJUPUT OIL 1.25 g/100 mL

Drug Label

DESCRIPTION

BENEFITS

A safe, all natural way to treat bacterial infections in saltwater fish and corals.

Use to treat open, red sores and wounds, fin and tail rot, eye cloud, pop eye, body slime and mouth fungus on fish.

API MARINE MELAFIX is also used in commercial coral farms to control bacterial infections, tissue degradation and for the removal of parasitic flatworms on wild corals.

May be used in all marine and reef aquariums.

Treating with MELAFIX will not harm the biological filter.

DIRECTIONS

Use dosing cap on bottle.

As a disease or wound treatment for marine fish and corals in the aquarium:

Remove activated carbon and turn off protein skimmer.

Shake Well.

Dose:

Add 5ml per 10 U.S. gallons (38 L) of aquarium water.

Dose daily for 7 days. After 7 days make a 25% water change.

Replace activated carbon and turn on protein skimmer.

The protein skimmer will collect excess foam.

Be prepared to dispose of the foam as it will be significant.

It may be necessary to turn down the protein skimmer for a few days until the foaming subsides.

As a coral dip:

Corals may be treated in small containers, and then placed in the aquarium.

Shake Well.

Dose:

Add 20 ml per 1/2 U.S. gallon (2 L) of aquarium water. Make sure the water temperature, pH, and salinity are correct. Place the coral in the water for 3-5 minutes.

Shake corals under water to help dislodge worms. After a maximum treatment time of 5 minutes, place the corals into the aquarium.

ACTIVE INGREDIENT: Melaleuca 1.25%

Warning:

This product contains a chemical known to the State of California to cause cancer or birth defects or other reproductive harm.

Keep out of reach of children.

For aquarium use only.

Treats up to 948 U.S. gallons (3,588) of salt water.

U.S. Patent 5,882,647; Patent EP 0861032; Other Patents issued.

Questions or Comments?

Call 1-800-847-0659 or visit us at www.apifishcare.com

www.facebook.com/apifishcare

PACKAGE LABEL

API

MARINE

MELAFIX

HEALS BACTERIAL INFECTIONS

Rapidly repairs damaged fins, ulcers and open wounds

Natural botanical extract

Reverses coral degradation

GUIDE

Fish Problem

Solving

16 FL OZ (473 ml)